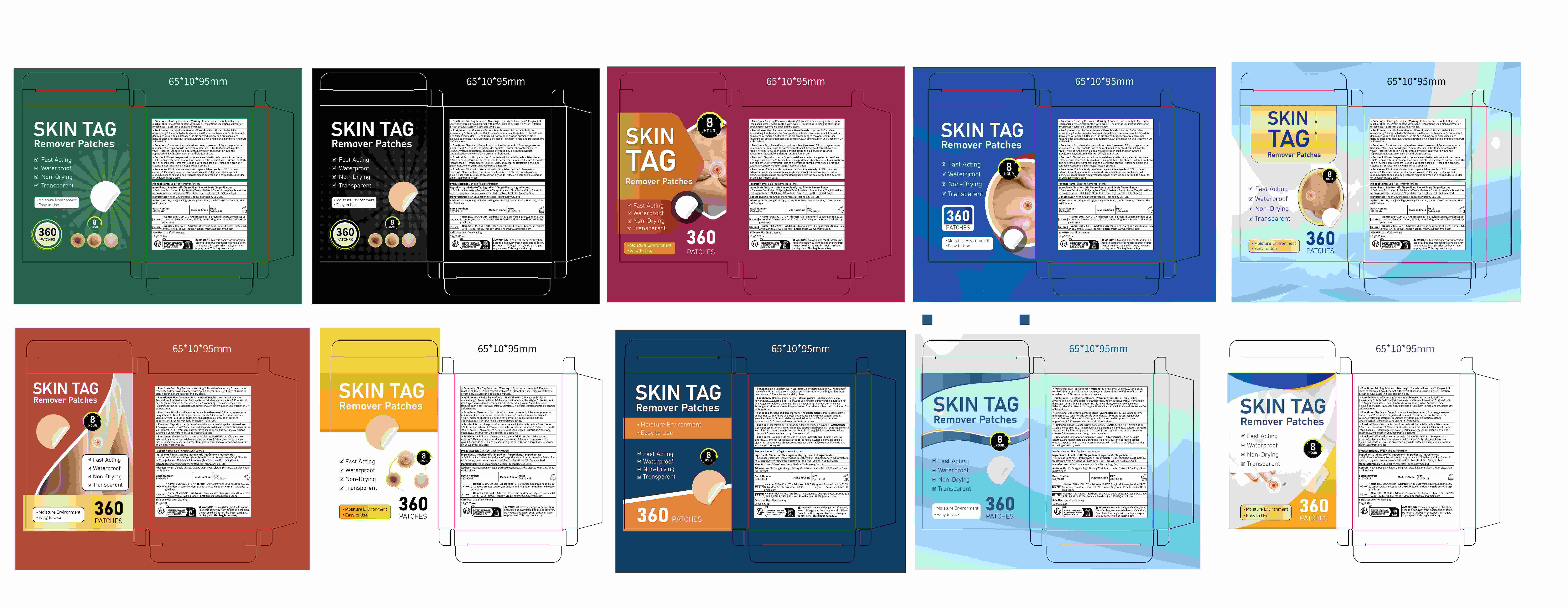 DRUG LABEL: Skin Tag Remover Patches
NDC: 84758-002 | Form: PATCH
Manufacturer: Xi'an Chuancheng Medical Technology Co., Ltd.
Category: otc | Type: HUMAN OTC DRUG LABEL
Date: 20240926

ACTIVE INGREDIENTS: SALICYLIC ACID 0.75 g/15 g
INACTIVE INGREDIENTS: CELLULOSE SULFATE 2 g/15 g; MELALEUCA ALTERNIFOLIA (TEA TREE) LEAF OIL 1 g/15 g; POLYETHYLENE TEREPHTHALATE (INTRINSIC VISCOSITY 0.40-0.70) 10 g/15 g; DIMETHICONE/VINYL DIMETHICONE CROSSPOLYMER (SOFT PARTICLE) 1.25 g/15 g

Active Ingredient

Salicylic Acid 5%

PURPOSE

Wart remover

How To Use

1. Prep your skin. Cleanse and dry pimple area.
2.Patch the tag. Leave on for 6-8 hours.
3.Watch it work. Peel off when patch turns white.

Warnings

Warnings: to avoid danger of suffocation.keep this plastic bag away from babies andchildren.do not use this bag incribs, beds carriages or play pens. this bag is not a toy.

Stop Use

Stop using and ask a doctor if a rash and/or irritationoccurs.

Close

DO NOT USE

on damaged or broken skin

WHEN USING

keep out of eyes. Rinse with water to remove.

Keep Oot Of Reach Of Children

If swallowed, get medical help or contact a Poison Control Center right away.

INACTIVE INGREDIENT

Cellulose Succinate
Polyethylene Terephthalate
Dimethicone/Vinyl Dimethicone Crosspolymer
Melaleuca Alternifolia (Tea Tree) Leaf Oil·

DOSAGE;Patch
Route of Administration:TOPCIAL